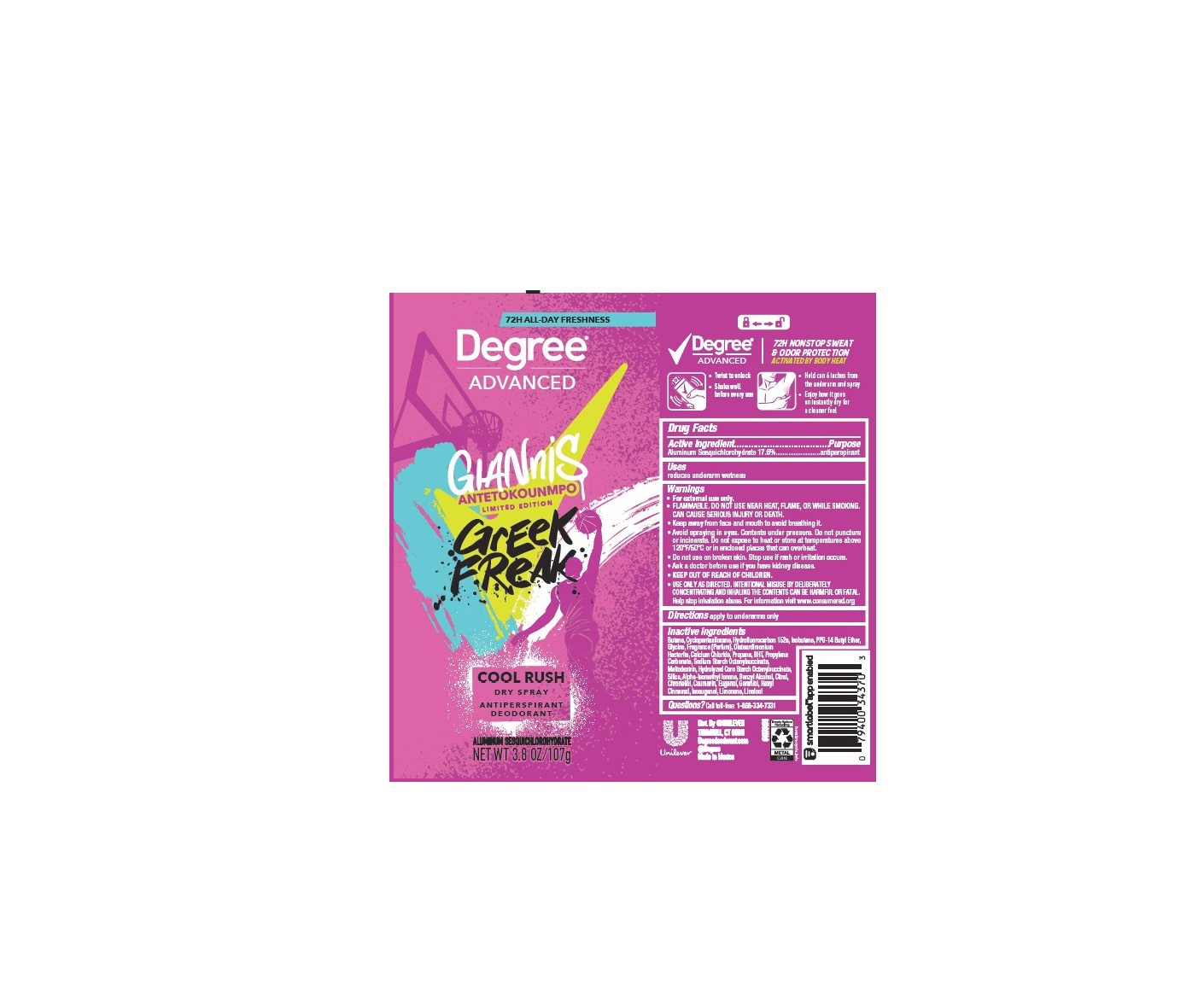 DRUG LABEL: Degree
NDC: 64942-2319 | Form: AEROSOL, SPRAY
Manufacturer: Conopco, Inc. d/b/a Unilever
Category: otc | Type: HUMAN OTC DRUG LABEL
Date: 20240716

ACTIVE INGREDIENTS: ALUMINUM SESQUICHLOROHYDRATE 17.6 g/100 g
INACTIVE INGREDIENTS: .ALPHA.-HEXYLCINNAMALDEHYDE; COUMARIN; GERANIOL; ISOMETHYL-.ALPHA.-IONONE; .BETA.-CITRONELLOL, (R)-; LINALOOL, (+/-)-; SILICON DIOXIDE; MALTODEXTRIN; PROPYLENE CARBONATE; GLYCINE; LIMONENE, (+)-; ISOBUTANE; CITRAL; BUTANE; 1,1-DIFLUOROETHANE; CYCLOMETHICONE 5; PPG-14 BUTYL ETHER; DISTEARDIMONIUM HECTORITE; CALCIUM CHLORIDE; PROPANE; BUTYLATED HYDROXYTOLUENE; BENZYL ALCOHOL; EUGENOL; ISOEUGENOL

Degree Advanced Greek Freak Cool Rush Dry Spray Antiperspirant Deodorant

Drug Facts

Active ingredient

Aluminum Sesquichlorohydrate (17.6%)

Purpose

antiperspirant

Uses

reduces underarm wetness

Directions

For underarms use only

Warnings

• FLAMMABLE. DO NOT USE NEAR HEAT, FLAME, OR WHILE SMOKING. CAN CAUSE SERIOUS INJURY OR DEATH.
• Keep away from face and mouth to avoid breathing in.
• Avoid spraying in eyes. Contents under pressure. Do not puncture or incinerate. Do not expose to heat or store at temperatures above 120°F/50°C or in enclosed places that could overheat.
• Do not use on broken skin. Stop use if rash or irritation occurs.
• Ask a doctor before using if you have kidney disease.
• USE ONLY AS DIRECTED. INTENTIONAL MISUSE BY DELIBERATELY CONCENTRATING AND INHALING THE CONTENTS CAN BE HARMFUL OR FATAL.
Help stop inhalation abuse. For information visit www.inhalant.org

• KEEP OUT OF REACH OF CHILDREN

Inactive ingredients

Butane, Cyclopentasiloxane, Hydrofluorocarbon 152a, Isobutane, PPG-14 Butyl Ether, Glycine, Fragrance (Parfum), Disteardimonium Hectorite, Calcium Chloride, Propane, BHT, Propylene Carbonate, Sodium Starch Octenylsuccinate, Maltodextrin, Hydrolyzed Corn Starch Octenylsuccinate, Silica, Alpha-Isomethyl Ionone, Benzyl Alcohol, Citral, Citronellol, Coumarin, Eugenol,Geraniol, Hexyl Cinnamal, Isoeugenol, Limonene, Linalool

Questions?

Call toll-free 1-866-334-7331